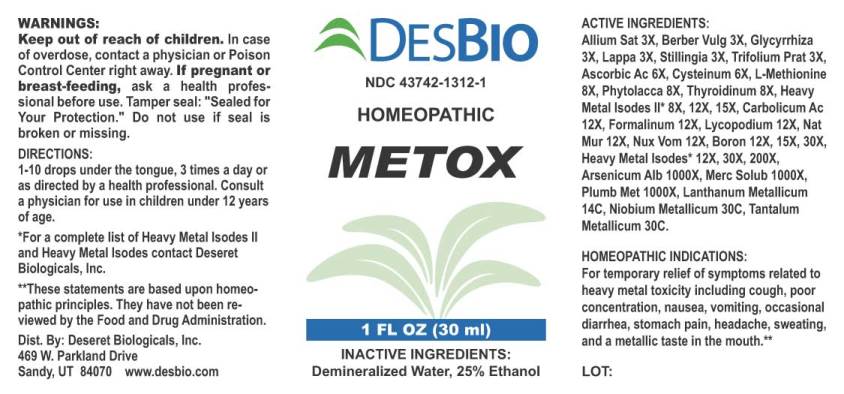 DRUG LABEL: Metox
NDC: 43742-1312 | Form: LIQUID
Manufacturer: Deseret Biologicals, Inc.
Category: homeopathic | Type: HUMAN OTC DRUG LABEL
Date: 20250527

ACTIVE INGREDIENTS: GARLIC 3 [hp_X]/1 mL; BERBERIS VULGARIS ROOT BARK 3 [hp_X]/1 mL; GLYCYRRHIZA GLABRA 3 [hp_X]/1 mL; ARCTIUM LAPPA ROOT 3 [hp_X]/1 mL; STILLINGIA SYLVATICA ROOT 3 [hp_X]/1 mL; TRIFOLIUM PRATENSE FLOWER 3 [hp_X]/1 mL; ASCORBIC ACID 6 [hp_X]/1 mL; CYSTEINE 6 [hp_X]/1 mL; METHIONINE 8 [hp_X]/1 mL; PHYTOLACCA AMERICANA ROOT 8 [hp_X]/1 mL; SUS SCROFA THYROID 8 [hp_X]/1 mL; TRIBASIC CALCIUM PHOSPHATE 8 [hp_X]/1 mL; CHROMIUM 8 [hp_X]/1 mL; COBALT 8 [hp_X]/1 mL; COPPER 8 [hp_X]/1 mL; IRON 8 [hp_X]/1 mL; IODINE 8 [hp_X]/1 mL; IRIDIUM 8 [hp_X]/1 mL; POTASSIUM CARBONATE 8 [hp_X]/1 mL; LITHIUM CARBONATE 8 [hp_X]/1 mL; MAGNESIUM 8 [hp_X]/1 mL; MANGANESE 8 [hp_X]/1 mL; MOLYBDENUM 8 [hp_X]/1 mL; SODIUM CHLORIDE 8 [hp_X]/1 mL; PHOSPHORUS 8 [hp_X]/1 mL; SELENIUM 8 [hp_X]/1 mL; STRONTIUM CARBONATE 8 [hp_X]/1 mL; SULFUR 8 [hp_X]/1 mL; VANADIUM 8 [hp_X]/1 mL; ZINC 8 [hp_X]/1 mL; PHENOL 12 [hp_X]/1 mL; FORMALDEHYDE 12 [hp_X]/1 mL; LYCOPODIUM CLAVATUM SPORE 12 [hp_X]/1 mL; STRYCHNOS NUX-VOMICA SEED 12 [hp_X]/1 mL; BORON 12 [hp_X]/1 mL; ALUMINUM 12 [hp_X]/1 mL; ANTIMONY TRISULFIDE 12 [hp_X]/1 mL; SILVER 12 [hp_X]/1 mL; ARSENIC TRIOXIDE 12 [hp_X]/1 mL; GOLD 12 [hp_X]/1 mL; BARIUM CARBONATE 12 [hp_X]/1 mL; BERYLLIUM 12 [hp_X]/1 mL; BISMUTH 12 [hp_X]/1 mL; BROMINE 12 [hp_X]/1 mL; CADMIUM 12 [hp_X]/1 mL; CERIUM 12 [hp_X]/1 mL; CESIUM CHLORIDE 12 [hp_X]/1 mL; DYSPROSIUM 12 [hp_X]/1 mL; ERBIUM 12 [hp_X]/1 mL; EUROPIUM 12 [hp_X]/1 mL; GADOLINIUM 12 [hp_X]/1 mL; GERMANIUM SESQUIOXIDE 12 [hp_X]/1 mL; HOLMIUM 12 [hp_X]/1 mL; INDIUM 12 [hp_X]/1 mL; MERCURIUS SOLUBILIS 12 [hp_X]/1 mL; NEODYMIUM OXIDE 12 [hp_X]/1 mL; NICKEL 12 [hp_X]/1 mL; OSMIUM 12 [hp_X]/1 mL; PALLADIUM 12 [hp_X]/1 mL; PLATINUM 12 [hp_X]/1 mL; LEAD 12 [hp_X]/1 mL; PRASEODYMIUM 12 [hp_X]/1 mL; RHODIUM 12 [hp_X]/1 mL; RUBIDIUM NITRITE 12 [hp_X]/1 mL; SAMARIUM 12 [hp_X]/1 mL; TIN 12 [hp_X]/1 mL; TERBIUM 12 [hp_X]/1 mL; THALLIUM 12 [hp_X]/1 mL; URANYL NITRATE HEXAHYDRATE 12 [hp_X]/1 mL; YTTERBIUM OXIDE 12 [hp_X]/1 mL; LANTHANUM 14 [hp_C]/1 mL; NIOBIUM 30 [hp_C]/1 mL; TANTALUM 30 [hp_C]/1 mL
INACTIVE INGREDIENTS: WATER; ALCOHOL

Drug Facts:

ACTIVE INGREDIENTS:

Allium Sativum 3X, Berberis Vulgaris 3X, Glycyrrhiza Glabra 3X, Lappa Major 3X, Stillingia Sylvatica 3X, Trifolium Pratense 3X, Ascorbicum Acidum 6X, Cysteinum 6X, L-Methionine 8X, Phytolacca Decandra 8X, Thyroidinum (Suis) 8X, Calcarea Phosphorica 8X, 12X, 15X, Chromium Metallicum 8X, 12X, 15X, Cobaltum Metallicum 8X, 12X, 15X, Cuprum Metallicum 8X, 12X, 15X, Ferrum Metallicum 8X, 12X, 15X, Iodium 8X, 12X, 15X, Iridium Metallicum 8X, 12X, 15X, Kali Carbonicum 8X, 12X, 15X, Lithium Carbonicum 8X, 12X, 15X, Magnesium Metallicum 8X, 12X, 15X, Manganum Metallicum 8X, 12X, 15X, Molybdenum 8X, 12X, 15X, Natrum Muriaticum 8X, 12X, 15X, Phosphorus 8X, 12X, 15X, Selenium Metallicum 8X, 12X, 15X, Strontium Carbonicum 8X, 12X, 15X, Sulphur 8X, 12X, 15X, Vanadium Metallicum 8X, 12X, 15X, Zincum Metallicum 8X, 12X, 15X, Carbolicum Acidum 12X, Formalinum 12X, Lycopodium Clavatum 12X, Natrum Muriaticum 12X, Nux Vomica 12X, Boron 12X, 15X, 30X, Aluminum Metallicum 12X, 30X, 200X, Antimonium Crudum 12X, 30X, 200X, Argentum Metallicum 12X, 30X, 200X, Arsenicum Album 12X, 30X, Aurum Metallicum 12X, 30X, 200X, Baryta Carbonica 12X, 30X, 200X, Beryllium Metallicum 12X, 30X, 200X, Bismuthum Metallicum 12X, 30X, 200X, Bromium 12X, 30X, 200X, Cadmium Metallicum 12X, 30X, 200X, Cerium Metallicum 12X, 30X, 200X, Cesium Chloride 12X, 30X, 200X, Dysprosium Metallicum 12X, 30X, 200X, Erbium Metallicum 12X, 30X, 200X, Europium Metallicum 12X, 30X, 200X, Gadolinium Metallicum 12X, 30X, 200X, Germanium Sesquioxide 12X, 30X, 200X, Holmium Metallicum 12X, 30X, 200X, Indium Metallicum 12X, 30X, 200X, Manganum Metallicum 12X, 30X, 200X, Mercurius Solubilis 12X, 30X, 200X, Neodymium Oxide 12X, 30X, 200X, Niccolum Metallicum 12X, 30X, 200X, Osmium Metallicum 12X, 30X, 200X, Palladium Metallicum 12X, 30X, 200X, Platinum Metallicum 12X, 30X, 200X, Plumbum Metallicum 12X, 30X, 200X, Praseodymium 12X, 30X, 200X, Rhodium Metallicum 12X, 30X, 200X, Rubidium Nitricum 12X, 30X, 200X, Samarium Metallicum 12X, 30X, 200X, Stannum Metallicum 12X, 30X, 200X, Terbium Metallicum 12X, 30X, 200X, Thallium Metallicum 12X, 30X, 200X, Uranium Nitricum 12X, 30X, 200X, Ytterbium Oxide 12X, 30X, 200X, Arsenicum Album 1000X, Mercurius Solubilis 1000X, Plumbum Metallicum 1000X, Lanthanum Metallicum 14C, Niobium Metallicum 30C, Tantalum Metallicum 30C.

HOMEOPATHIC INDICATIONS:

For temporary relief of symptoms related to heavy metal toxicity including cough, poor concentration, nausea, vomiting, occasional diarrhea, stomach pain, headache, sweating, and a metallic taste in the mouth.**

**These statements are based upon homeopathic principles. They have not been reviewed by the Food and Drug Administration.

WARNINGS:

Keep out of reach of children. In case of overdose, contact a physician or Poison Control Center right away.

If pregnant or breast-feeding, seek advice of a health professional before use.

Tamper seal: "Sealed for Your Protection." Do not use if seal is broken or missing.

Keep out of reach of children. In case of overdose, contact a physician or Poison Control Center right away.

DIRECTIONS:

1-10 drops under the tongue, 3 times a day or as directed by a health professional. Consult a physician for use in children under 12 years of age.

HOMEOPATHIC INDICATIONS:

For temporary relief of symptoms related to heavy metal toxicity including cough, poor concentration, nausea, vomiting, occasional diarrhea, stomach pain, headache, sweating, and a metallic taste in the mouth.**

**These statements are based upon homeopathic principles. They have not been reviewed by the Food and Drug Administration.

INACTIVE INGREDIENTS:

Demineralized Water, 25% Ethanol

QUESTIONS:

Dist. By: Deseret Biologicals, Inc.

469 W. Parkland Drive

Sandy, UT 84070 www.desbio.com

**For a complete list of Heavy Metal Isodes II and Heavy Metal Isodes contact Deseret Biologicals, Inc.

PACKAGE LABEL DISPLAY:

DESBIO

NDC 43742-1312-1

HOMEOPATHIC

METOX

1 FL OZ (30 ml)